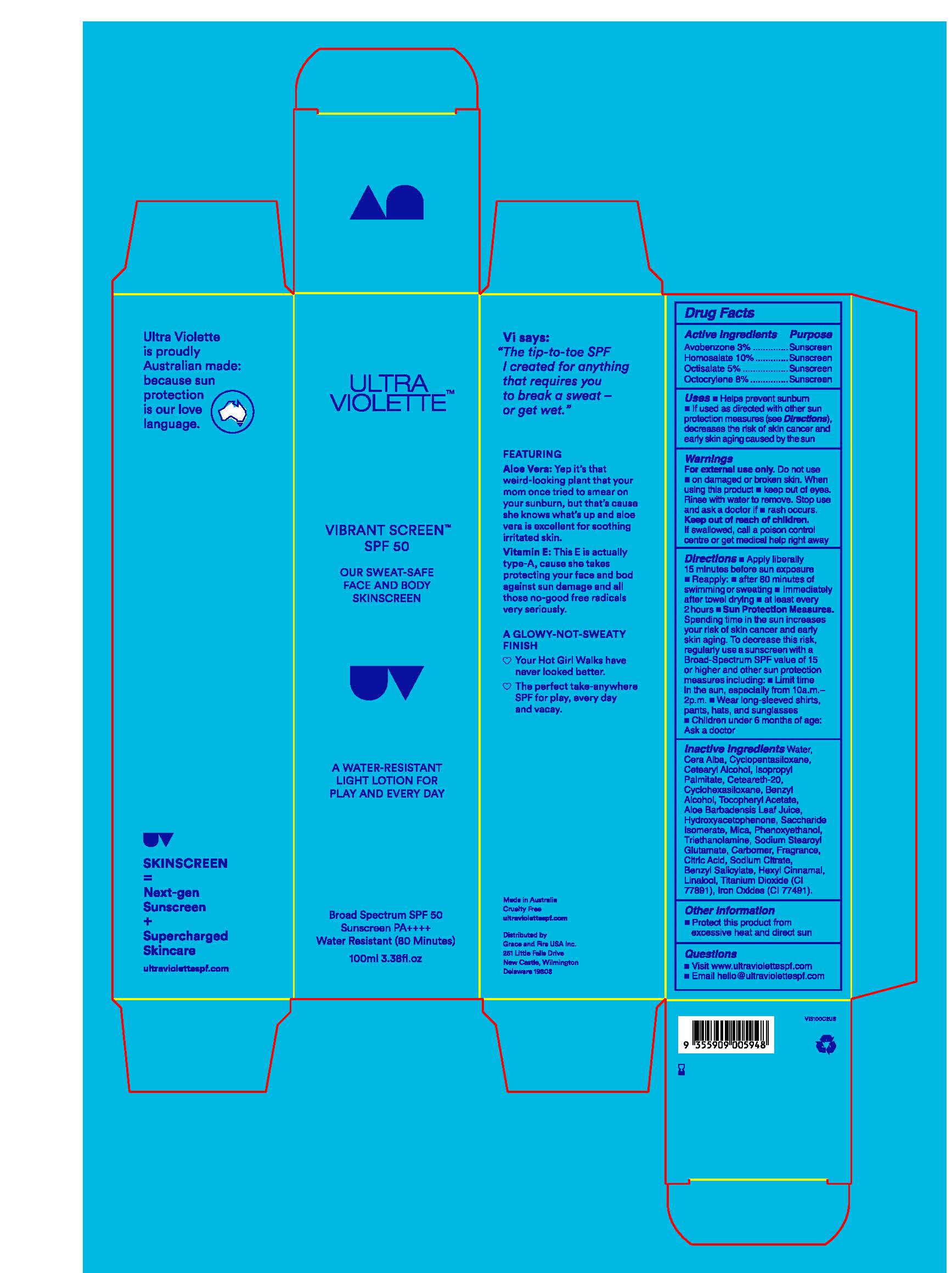 DRUG LABEL: Ultra Violette Vibrant Screen Broad Spectrum SPF 50
NDC: 84803-102 | Form: CREAM
Manufacturer: Grace and Fire USA Inc.
Category: otc | Type: HUMAN OTC DRUG LABEL
Date: 20260105

ACTIVE INGREDIENTS: AVOBENZONE 30 mg/1 mL; OCTOCRYLENE 80 mg/1 mL; OCTISALATE 50 mg/1 mL; HOMOSALATE 100 mg/1 mL
INACTIVE INGREDIENTS: ISOPROPYL PALMITATE; BENZYL SALICYLATE; LINALOOL, (+/-)-; CETEARETH-20; WATER; CYCLOPENTASILOXANE; BENZYL ALCOHOL; ALOE BARBADENSIS LEAF JUICE; SACCHARIDE ISOMERATE; MICA; TRIETHANOLAMINE; SODIUM STEAROYL GLUTAMATE; CARBOMER; CI 77891; WHITE WAX; PHENOXYETHANOL; CITRIC ACID; SODIUM CITRATE; CETEARYL ALCOHOL; ALPHA-TOCOPHEROL ACETATE; CI 77491; HYDROXYACETOPHENONE; HEXYL CINNAMAL

ACTIVE INGREDIENTS

AVOBENZONE 3.0%
HOMOSALATE 10%
OCTISALATE 5.0%
OCTOCRYLENE 8.0%

USE

HELPS PREVENT SUNBURN

if used as directed with other sun protections measures (see Directions), decreases the risk of skin cancer and early skin aging caused by the sun

WARNINGS

Do not use

on damaged or broken skin

When using this product

Keep out of eyes. Rinse with water to remove

Stop use and ask a doctor if

rash occurs

Keep out of reach of children

If swallowed, get medical help or contac a Poison Control Center right away

Directions

Directions for Sunscreen Use

apply liberally and evenly 15 minutes before sun exposure

reapply at least every 2 hours

use a water resistant sunscreen if swimming or sweating

Sun Protection Measures. Spending time in the sun increases your risk of skin cancer and early skin aging. To decrease this risk, regularly use a sunscreen with a Broad Spectrum SPF value of 15 or higher and other sun protection measures including:

limit time in the sun, especially from 10 a.m. – 2 p.m.

wear long-sleeved shirts, pants, hats, and sunglasses

children under 6 months of age: Ask a doctor

Inactive Ingredients

Water, Cera Alba, Cyclopentasiloxane, Cetearyl Alcohol, Isopropyl Palmitate, Ceteareth-20, Cyclohexasiloxane, Benzyl Alcohol, Tocopheryl Acetate, Aloe Barbadensis Leaf Juice, Hydroxyacetophenone, Saccharide Isomerate, Mica, Phenoxyethanol, Triethanolamine, Sodium Stearoyl Glutamate, Carbomer, Fragrance, Citric Acid, Sodium Citrate, Benzyl Salicylate, Hexyl Cinnamal, Linalool, Titanium Dioxide (CI 77891), Iron Oxides (CI 77491).

Other information

Other information protect the product in this container from excessive heat and direct sun